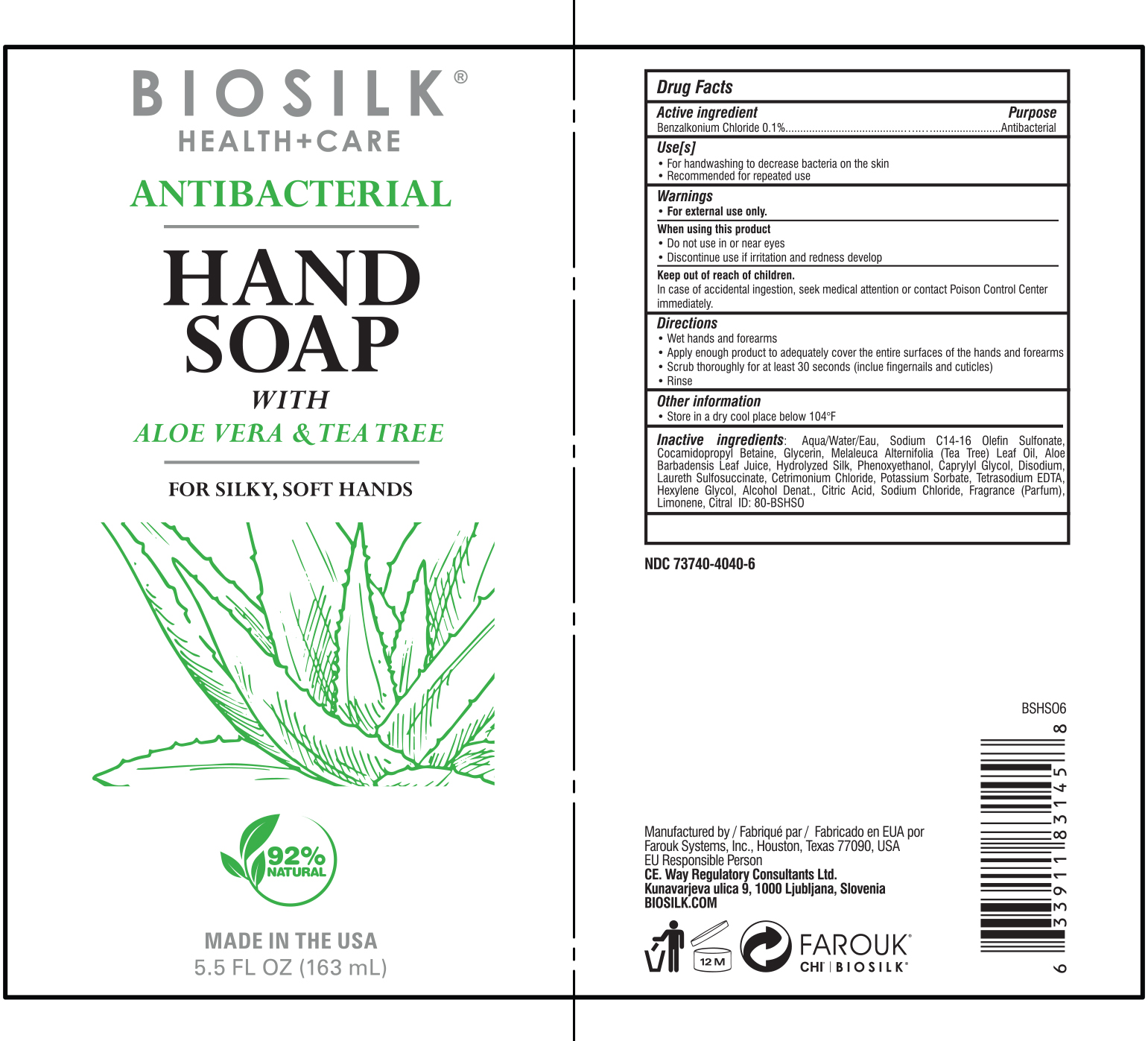 DRUG LABEL: Biosilk
NDC: 73740-4040 | Form: SOAP
Manufacturer: Farouk Systems, Inc.
Category: otc | Type: HUMAN OTC DRUG LABEL
Date: 20200331

ACTIVE INGREDIENTS: BENZALKONIUM 0.1 g/100 g
INACTIVE INGREDIENTS: ALCOHOL 0.011 g/100 g; WATER 88.5419 g/100 g; ANHYDROMETHYLENECITRIC ACID 0.001 g/100 g; LIMONENE, (+)- 0.1755 g/100 g; GLYCERIN 1.5 g/100 g; FRAGRANCE LAVENDER & CHIA F-153480 0.0915 g/100 g; ALOE VERA LEAF 0.001 g/100 g; SODIUM CHLORIDE 0.5 g/100 g; ETIDRONATE TETRASODIUM 0.084 g/100 g; SILK, ACID HYDROLYZED (1000 MW) 0.0011 g/100 g; PHENOXYETHANOL 0.4 g/100 g; CAPRYLYL GLYCOL 0.4 g/100 g; CETRIMONIUM CHLORIDE 0.2 g/100 g; POTASSIUM SORBATE 0.1 g/100 g; HEXYLENE GLYCOL 0.05 g/100 g; CITRAL 0.033 g/100 g; COCAMIDOPROPYL BETAINE 3.5 g/100 g; SODIUM C14-16 OLEFIN SULFONATE 4 g/100 g; DISODIUM LAURETH SULFOSUCCINATE 0.3 g/100 g; MELALEUCA ALTERNIFOLIA LEAF 0.01 g/100 g

BioSilk Foam Hand Antibacterial Soap

Inactive ingredients

Inactive infedients: Aqu,JWater/Eau, Sodium C14-16 Olefin Sulfonate,
Cocamidopropy Betaine, Glycenn, Melaleuca Alternifolia gea Tre Leaf Oil, Aloe Bart>adensis Leaf
Juice, Hydrolyzed Silk, Phenoxyehtanol, aprylyl lycol, Disodium, Laureth
Sulfosuccinate,Cetrimonium Chloride, Potassium Sorbate, TetrasodiumEDTA, Hexylene Glycol, Alcohol
Denat., Citric Acid, Sodium Chloride, Fragrance (Partum), Limonene, Cltral ID: 80-BSHSO

Active Ingredient

Active ingredient Purpose
Benzalkonium Chloride0.1% .................................................. ........ ....... ....
Antibacterial

Keep out of reach of Children

Incase of accidental ingestion, seek medical attention or contact Poison Control Center
immediately.

Purpose

Uses

For handwashing to decrease bacteria on the skjin

Recommended for repeated use

Indications & Usage

Use[s[
•For handwashing to decrease bacteria on the skin
•Recommended for repeated use

Directions
•Wethandsandforearms
•Applyenoughproducttoadequatelycovertheenliresurfacesofthehandsandforearms
•Scrublhoroughlyforatleast30seconds(incluefingernailsandculicles)
•Rinse

Warnings

•ForBIIBrnaluseonly.
Whan using this product
• Donotuseinorneareyes
•Discontinueuseifirritationandrednessdevelop
Keepoutolreacholchildren.
lncaseofaccidentalingestion,seekmedicalattentionorcontactPoisonContmlCenter immediately.

Storage and Handling

Other information
•Storeinadrycoolplacel:lelow104"f

Dosage & Administration

Active ingredient Purpose
BenzalkoniumChloride0.1%
.....................................................................Antibacterial

Directions
•Wethandsandforearms
•Applyenoughproducttoadequatelycovertheenliresurfacesofthehandsandforearms
•Scrublhoroughlyforatleast30seconds(incluefingernailsandculicles)
•Rinse

Principal Display Panel

BIOSILK®
HEALTH+CARE
ANTIBACTERIAL
HAND
SOAP
WITH
ALOE VERA &_TEA TREE

FOR SILKY, SOFT HANDS

92% Natural

MADE IN THE USA
11.5 FL OZ (340 ml)